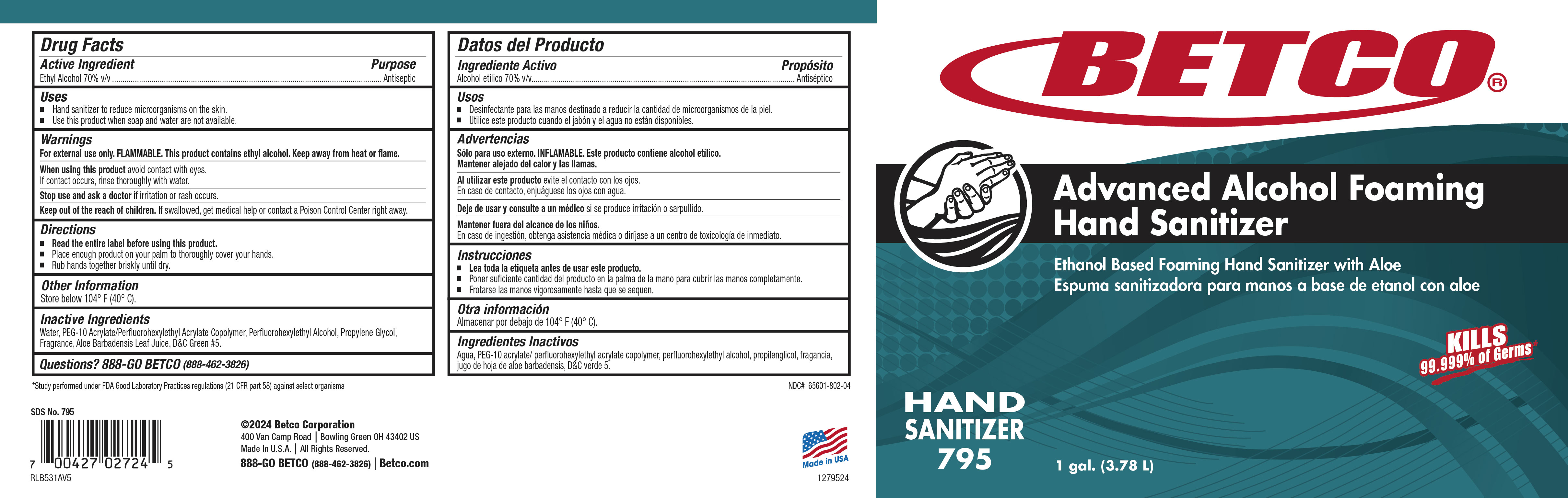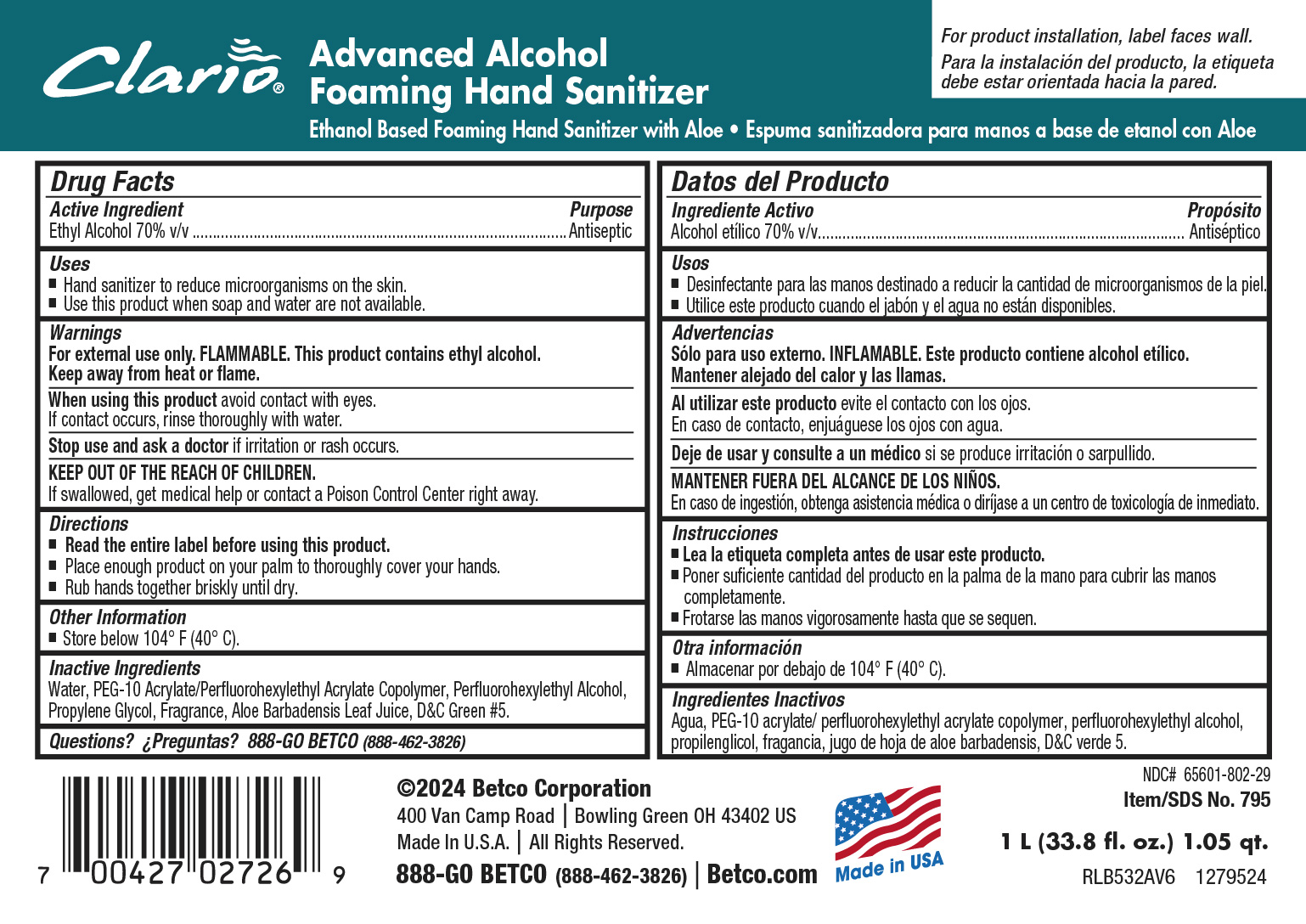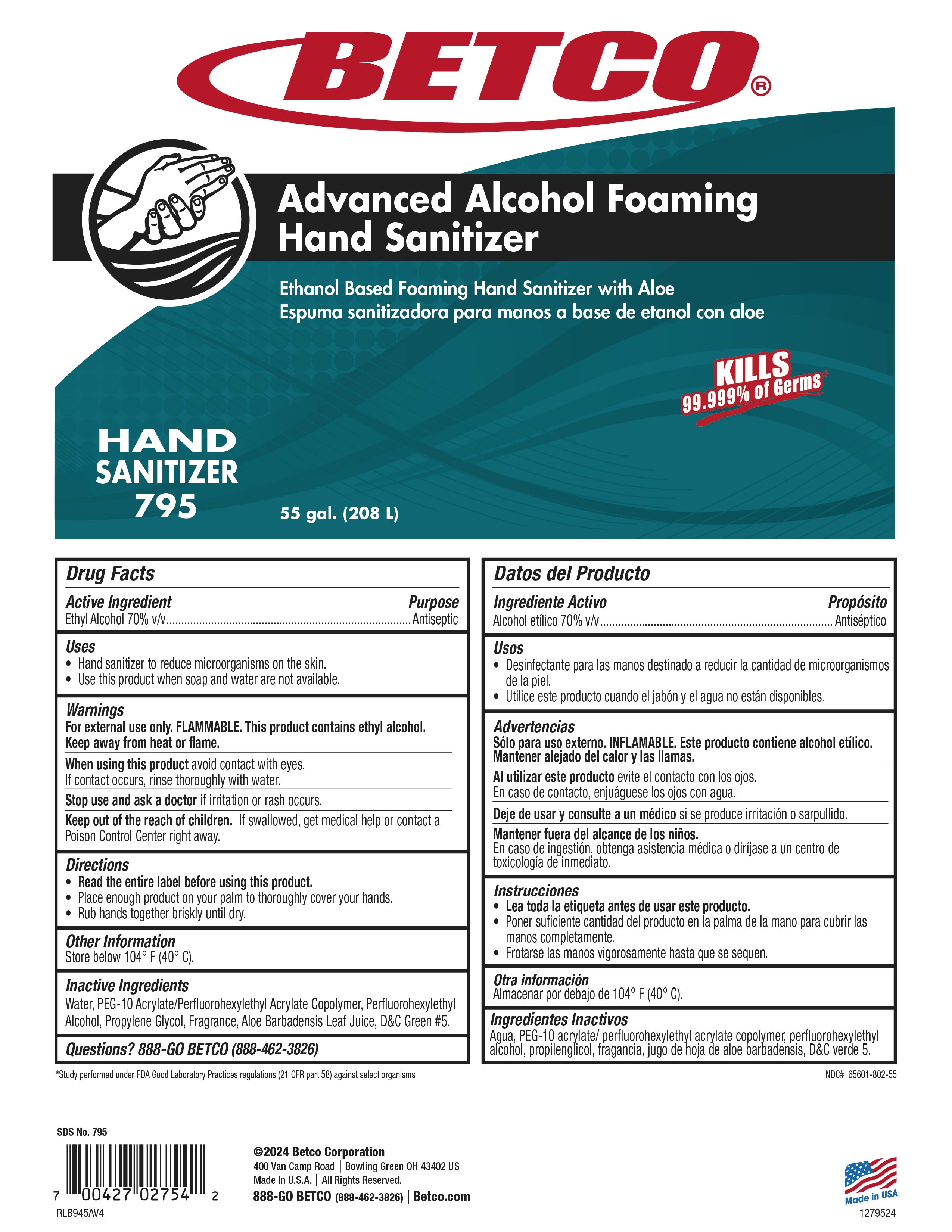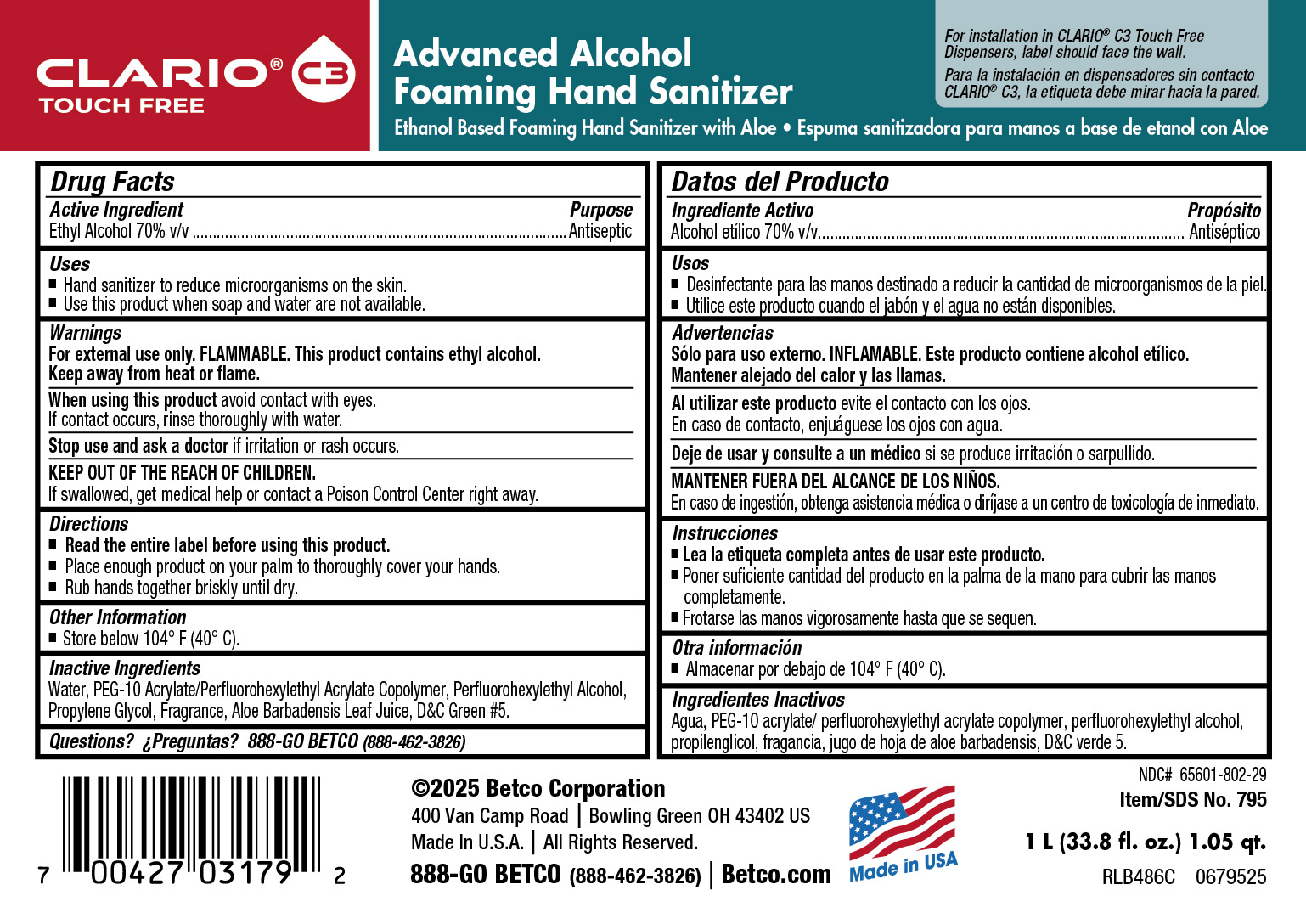 DRUG LABEL: Advanced Alcohol Foaming Hand Sanitizer
NDC: 65601-802 | Form: LIQUID
Manufacturer: Betco Corporation LLC
Category: otc | Type: HUMAN OTC DRUG LABEL
Date: 20260217

ACTIVE INGREDIENTS: ALCOHOL 0.6787 mL/1 mL
INACTIVE INGREDIENTS: HEXYL ACETATE; 4-CYCLOHEXYL-2-METHYL-2-BUTANOL; HYDROXYCITRONELLAL; D&C GREEN NO. 5 0.000002 mL/1 mL; WATER 0.2926 mL/1 mL; PROPYLENE GLYCOL 0.25 mL/1 mL; ALOE VERA LEAF 0.001 mL/1 mL; PEG-10 ACRYLATE/PERFLUOROHEXYLETHYL ACRYLATE COPOLYMER 0.5 mL/1 mL; 2-(PERFLUOROHEXYL)ETHANETHIOL 0.5 mL/1 mL; TETRAHYDROLINALOOL; ISOPROPYLPHENYLBUTANAL; EBANOL; 2-SEC-BUTYL CYCLOHEXANONE

advanced alcohol foaming sanititizer 65601-802

ACTIVE INGREDIENT

Ethjyl Alcohol

inactives

Aloe Barbadensis Leaf Juice, D&C Green #5, PEG 10 Perfluorohexylethyl acrylate copolymer, Perluorohexylethyl alcohol, propylene glycol, water

dosage

Please read entire label before using thsi product. Place enough product on your palm to tnoroughly cover your hands, Rub hands together briskyl until dry.

usage

Hand sanitizer to reduce mocroorganisms on the skin.. Use this product when soap and water are not available.

purpose

Antiseptic

Keep out of reach of children. If swallowed get medical help or contact a Poison Control center right away.

warnings

For external use only. FLAMMABLE. This product contains ethyl alcohol. Keep away from heat or flame.

When using this product avoid contact with eyes. If contact occurs rinse thoroughly with water.

Stop use and ask a doctor if irritation or rash occurs.